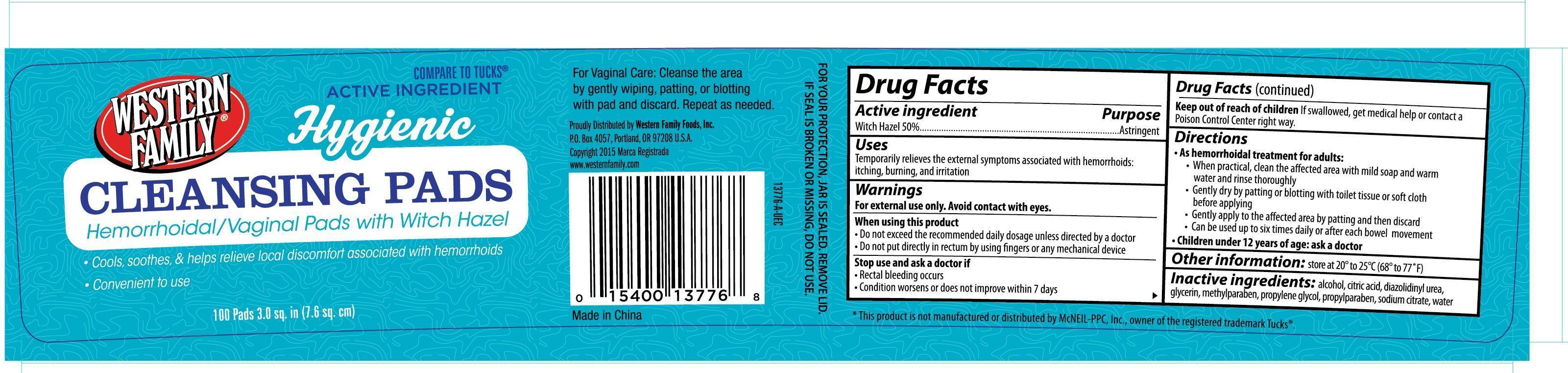 DRUG LABEL: Western Family Hygienic Cleansing
NDC: 55312-776 | Form: CLOTH
Manufacturer: Western Family Foods, Inc
Category: otc | Type: HUMAN OTC DRUG LABEL
Date: 20150710

ACTIVE INGREDIENTS: WITCH HAZEL 0.5 g/1 1
INACTIVE INGREDIENTS: ALCOHOL; DIAZOLIDINYL UREA; GLYCERIN; METHYLPARABEN; PROPYLENE GLYCOL; PROPYLPARABEN; SODIUM CITRATE; WATER

Active ingredient Purpose

Witch Hazel 50%......................................... Astringent

Uses

Temporarily relieves the external symptoms associated with hemorrhoids: itching, burning, and irritation

Warnings

For external use only. Avoid contact with eyes.

When using this product

- Do not exceed the recommended daily dosage unless directed by a doctor
- Do not put directly in rectum by using fingers or any mechanical device

Stop use and ask a doctor if

- Rectal bleeding occurs
- Condition worsens or does not improve within 7 days

Keep out of reach of children. If swallowed, get medical help or contact a Poision Control Center right away.

Directions

- As hemorrhoidal treatment for adults:
- When practical, clean the affected area with mild soap and warm water and rinse thoroughly
- Gently dry by patting or blotting with toilet tissue or soft cloth before applying
- Gently apply to the affected area by patting and then discard
- Can be used up to six times daily or after each bowel movement

ASK DOCTOR

Children under 12 years of age: ask a doctor

Other information: store at 20° to 25°C (68° to 77°F)

INACTIVE INGREDIENT

Inactive ingredients: alcohol, citric acid, diazolidinyl urea, glycerin, methylparaben, propylene glycol, propylparaben, sodium citrate, water

DOSAGE AND ADMINISTRATION

Distributed by:

Western Family Foods, Inc.

P.O. Box 4057

Portland, OR 97208 USA

www.westernfamily.com

Made in China